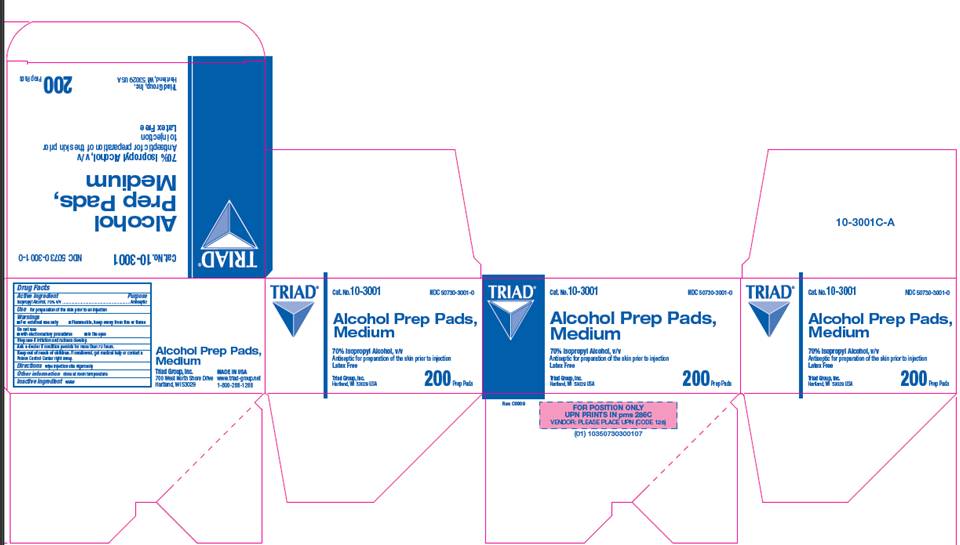 DRUG LABEL: Isopropyl alcohol
NDC: 50730-3001 | Form: SWAB
Manufacturer: H and P Industries, Inc. dba Triad Group
Category: otc | Type: HUMAN OTC DRUG LABEL
Date: 20091113

ACTIVE INGREDIENTS: Isopropyl alcohol .7 mL/1 1
INACTIVE INGREDIENTS: water

DRUG FACTS

ACTIVE INGREDIENT

Isopropyl Alcohol 70% v/v

PURPOSE

Antiseptic

USE

- For preparation of the skin prior to injection

WARNINGS

- For external use only

- Flammable, keep away from fire or flame

DO NOT USE

- With electrocautery procedures
- In the eyes

ASK A DOCTOR

if condition persists for more than 72 hours

STOP USE

if irritation and redness develop

KEEP OUT OF REACH OF CHILDREN

If swallowed, get medical help or contact a Poison Control Center right away.

DIRECTIONS

Wipe injection site vigorously.

OTHER INFORMATION

Store at room temperature

INACTIVE INGREDIENT

water

PACKAGE INFORMATION

TRIAD
Cat. No. 10-3001
NDC 50730-3001-0
Alcohol Prep Pads, Medium
70% Isopropyl Alcohol, v/v
Antiseptic for preparation of the skin prior to injection
Latex Free
200 Prep Pads
Triad Group, Inc.
700 West North Shore Drive
Hartland, WI 53029
MADE IN USA
www.triad-group.net
1-800-288-1288